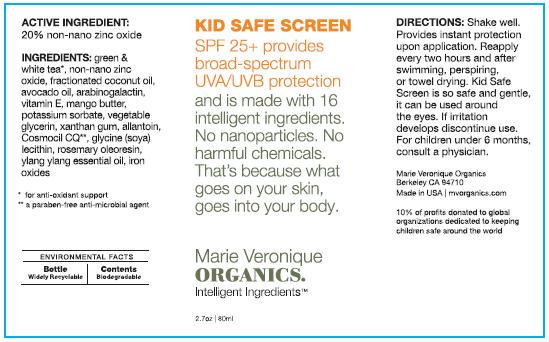 DRUG LABEL: Kid Safe Screen
NDC: 62742-4054 | Form: CREAM
Manufacturer: Allure Labs, Inc.
Category: otc | Type: HUMAN OTC DRUG LABEL
Date: 20171221

ACTIVE INGREDIENTS: ZINC OXIDE 200 mg/1 mL
INACTIVE INGREDIENTS: COCONUT OIL; AVOCADO OIL; TOCOPHEROL; POTASSIUM SORBATE; GLYCERIN; XANTHAN GUM; ALLANTOIN; GLYCINE; ROSEMARY OIL

Drug Facts

ACTIVE INGREDIENT:

20% non-nano zinc oxide

INACTIVE INGREDIENTS:

green and white tea, fractioned coconut oil, avocado oil, arabinogalactin, vitamin E, mango butter, potassium sorbate, vegetable glycerin, xanthan gum, allantoin, Cosmocil CQ, glycine (soya) lecithin, rosemary oleoresin, ylang ylang essential oil, iron oxides

green and white tea for anti-oxidant support

Cosmocil CQ, a paraben-free anti-microbial agent

DIRECTIONS:

Shake well.
Provides instant protection upon application.
Reapply every two hours and after swimming, perspiring, or towel drying.
Kid Safe Screen is so safe and gentle, it can be used around the eyes.

If irritation develops discontinue use.

For children under 6 months, consult a physician.

OTHER INFORMATION:

ENVIRONMENTAL FACTS

Bottle Widely Recyclable I Content Biodegradable

10% of profits donated to global organizations dedicated to keeping children safe around the world.

DISTRIBUTOR:

Marie Veronique Organics
Berkeley CA 94710

Made in USA

mvorganics.com

PACKAGE LABEL

KID SAFE SCREEN

SPF 25+ provides broad-spectrum UVA/UVB protection and is made with 16 intelligent ingredients. No nanoparticle. No harmful chemicals. That's because what goes on your skin, goes into your body.

Marie Veronique
ORGANICS
Intelligent Ingredients

2.7oz / 80ml